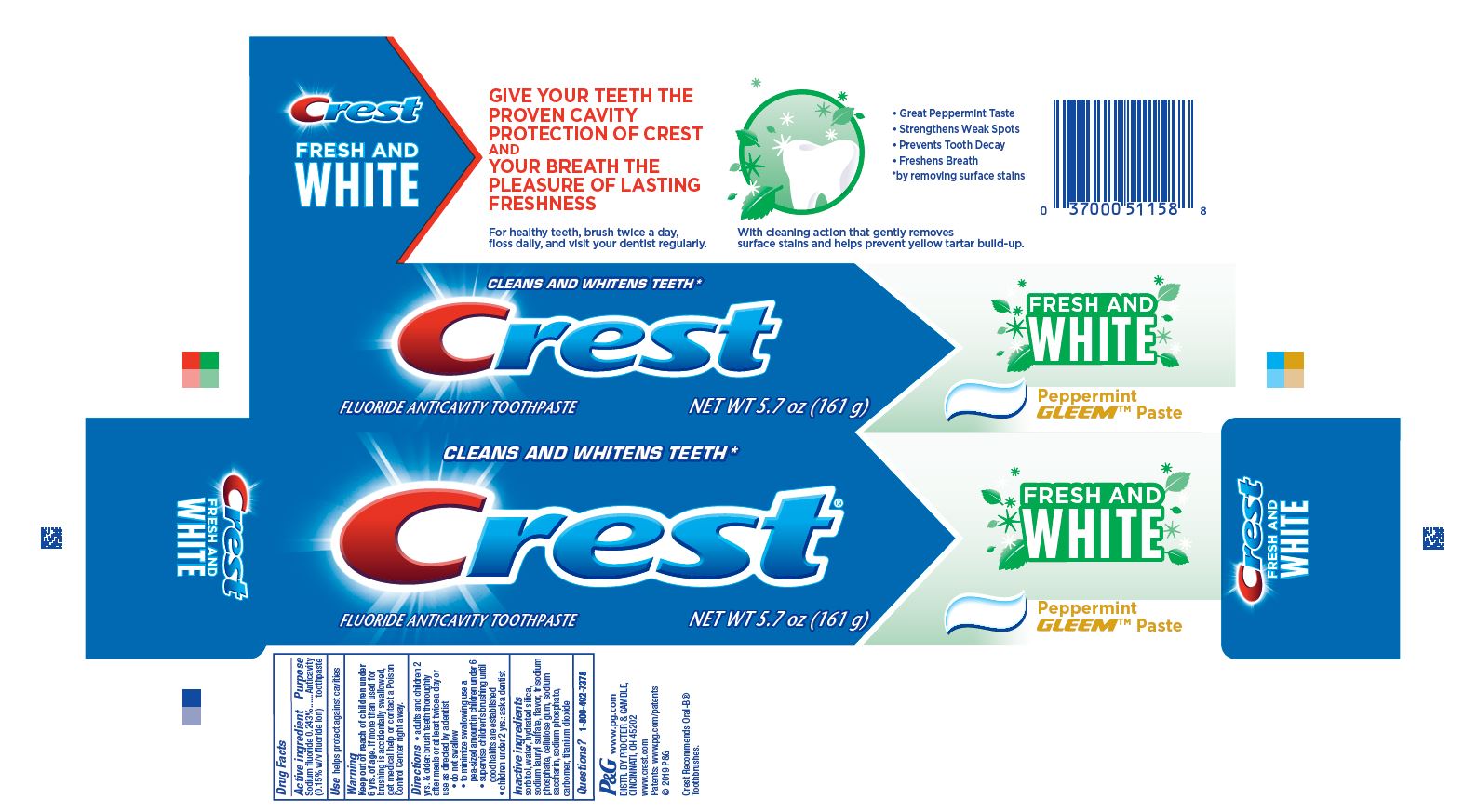 DRUG LABEL: Crest
NDC: 69423-897 | Form: PASTE, DENTIFRICE
Manufacturer: The Procter & Gamble Manufacturing Company
Category: otc | Type: HUMAN OTC DRUG LABEL
Date: 20250806

ACTIVE INGREDIENTS: SODIUM FLUORIDE 1.5 mg/1 g
INACTIVE INGREDIENTS: CARBOXYPOLYMETHYLENE; SODIUM PHOSPHATE; SORBITOL; WATER; HYDRATED SILICA; SODIUM LAURYL SULFATE; SACCHARIN SODIUM; CARBOXYMETHYLCELLULOSE SODIUM, UNSPECIFIED FORM; TITANIUM DIOXIDE; SODIUM PHOSPHATE, TRIBASIC, ANHYDROUS

Crest Fresh and White Peppermint Gleem Toothpaste

Drug Facts

Active ingredient

Sodium fluoride 0.243% (0.15% w/v fluoride ion)

Purpose

Anticavity toothpaste

Use

helps protect against cavities

Warning

Keep out of reach of children under 6 yrs. of age. If more than used for brushing is accidentally swallowed, get medical help or contact a Poison Control Center right away.

Directions

- adults and children 2 yrs. & older: brush teeth thoroughly after meals or at least twice a day or use as directed by a dentist
  - do not swallow
  - to minimize swallowing use a pea-sized amount in children under 6
  - supervise children's brushing until good habits are established
- children under 2 yrs.: ask a dentist

Inactive ingredients

sorbitol, water, hydrated silica, sodium lauryl sulfate, flavor, trisodium phosphate, cellulose gum, sodium saccharin, sodium phosphate,
carbomer, titanium dioxide

Questions?

1-800-492-7378

Distr. by Procter & Gamble, Cincinnati, OH 45202

PRINCIPAL DISPLAY PANEL - 161 g Tube Carton

CLEANS AND WHITENS TEETH*

Crest®

FLUORIDE ANTICAVITY TOOTHPASTE

NET WT 5.7 oz (161 g)

FRESH AND WHITE

Peppermint

GLEEM™ Paste